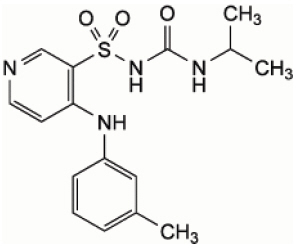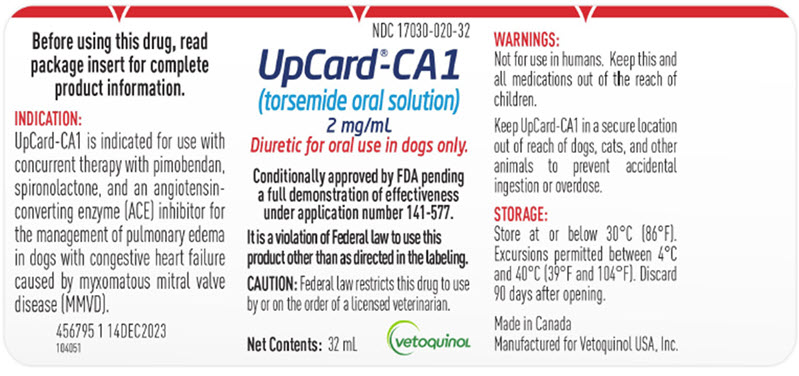 DRUG LABEL: UpCArd-CA1 
NDC: 17030-020 | Form: SOLUTION
Manufacturer: Vetoquinol USA, Inc.
Category: animal | Type: PRESCRIPTION ANIMAL DRUG LABEL
Date: 20240510

ACTIVE INGREDIENTS: TORSEMIDE 2 mg/1 mL

UpCard®-CA1
(torsemide oral solution)

2 mg/mL
Diuretic for oral use in dogs only.

Conditionally approved by FDA pending a full demonstration of effectiveness under application number 141-577.

It is a violation of Federal law to use this product other than as directed in the labeling.

Caution:

Federal law restricts this drug to use by or on the order of a licensed veterinarian. Use only as directed.

Description:

UpCard-CA1 (torsemide oral solution) is a loop diuretic of the pyridyl sulfonylurea class. Loop diuretics mainly inhibit the Na+/2Cl-/K+ carrier in the ascending limb of the loop of Henle. UpCard-CA1 is an oral solution of 0.2% w/v torsemide in an aqueous mixture containing tromethamine, hydroxyethyl cellulose, saccharin sodium, and propylene glycol.

Torsemide has the structural formula:

Molecular Formula: C16H20N4O3S
Molecular Weight: 348.42

Indication:

UpCard-CA1 is indicated for use with concurrent therapy with pimobendan, spironolactone, and an angiotensin converting enzyme (ACE) inhibitor for the management of pulmonary edema in dogs with congestive heart failure caused by myxomatous mitral valve disease (MMVD).

Dosage and Administration:

UpCard-CA1 should be administered orally once daily at a dose of 0.05 to 0.2 mg/lb (0.11 to 0.44 mg/kg) of bodyweight, corresponding to 0.025 to 0.10 mL/lb (0.055 to 0.22 mL/kg).

UpCard-CA1 is intended for long term administration at a dose adapted to the severity of clinical signs of pulmonary edema, results of physical examination, hydration status, and blood urea nitrogen (BUN), serum creatinine, and serum electrolyte levels.

Do not exceed a dose of 0.2 mg/lb (0.44 mg/kg) per day, corresponding to 0.1 mL/lb (0.22 mL/kg).

UpCard-CA1 may be administered with or without food.

UpCard-CA1 Dose Adjustment:

Long term diuretic therapy with UpCard-CA1 should be continued at the lowest effective dose. The dosage should be adjusted to maintain patient comfort, and control clinical signs based on serial physical examination and clinical pathology evaluation performed regularly during the early course of therapy and periodically thereafter (see Precautions).

The dose of UpCard-CA1 may be increased or decreased within the recommended dose range by increments of 25% of the administered dose under veterinary supervision.

Contraindications:

Do not administer UpCard-CA1 to dogs with renal failure or anuria. Therapy should be discontinued in dogs with progressive renal disease if increasing azotemia and oliguria occur during the therapy.

Do not administer UpCard-CA1 to dogs with severe dehydration, hypovolemia or hypotension.

Do not administer UpCard-CA1 concomitantly with other loop diuretics (e.g., furosemide).

Do not administer UpCard-CA1 to dogs with hypersensitivity to the active substance, torsemide, or to any of the excipients.

Warnings:

SAFE HANDLING WARNING

User Safety Warnings: Not for use in humans. Keep this and all medications out of the reach of children. Wash hands after use and/or spillage.

In case of accidental human ingestion, seek medical advice immediately and show package insert or the label to the physician. Symptoms of exposure to torsemide may include dryness of the mouth, thirst, weakness, lethargy, drowsiness, restlessness, muscle pains or cramps, muscular fatigue, hypotension, oliguria, tachycardia, nausea, or vomiting. Additionally, exposure may induce hypovolemia and result in hyperglycemia, hypokalemia, shunt thrombosis, syncope, and ventricular tachycardia.

Animal Safety Warnings:

Keep UpCard-CA1 in a secure location out of reach of dogs, cats, and other animals to prevent accidental ingestion or overdose.

In case of accidental overdose, provide drinking water and monitor electrolytes. Symptomatic therapy (e.g., fluid therapy) should be provided as medically necessary.

The administration of UpCard-CA1, a loop diuretic, may lead to excessive diuresis which could result in electrolyte imbalance, dehydration, and reduction of plasma volume enhancing the risk of circulatory collapse, thrombosis, and embolism. Dogs receiving UpCard-CA1 should be observed for signs of fluid depletion with electrolyte imbalance.

Precautions:

UpCard-CA1 is not indicated for dogs presenting in acute crisis with pulmonary edema, pleural effusion, and/or ascites requiring emergency treatment. The use of injectable diuretic therapy should be considered first in dogs presenting in acute crisis before commencing oral therapy with UpCard-CA1.

UpCard-CA1 is for use only in stable dogs with congestive heart failure caused by MMVD. A diagnosis of MMVD should be made by means of a comprehensive physical and cardiac examination.

Pre-existing electrolyte abnormalities and/or dehydration should be corrected prior to therapy with UpCard-CA1.

The safe administration of UpCard-CA1 relies on regular assessment of treated dogs for the clinical signs of pulmonary edema and potential treatment-related adverse events. Physical examination, hydration status, BUN, serum creatinine, and serum electrolytes should be assessed prior to the initiation of therapy or dose adjustment, and at 24 hours and 48 hours after the start of therapy or dose adjustment. These parameters should be monitored on a monthly basis until they are stable.

Carefully monitor the electrolyte status in cases of concomitant use with products affecting electrolyte balance (e.g., corticosteroids, amphotericin B, and cardiac glycosides).

Concurrent use of drugs that increase the risk of renal injury or renal insufficiency should be avoided.

Concurrent use of non-steroidal anti-inflammatory drugs (NSAIDs) with UpCard-CA1 may result in a decreased natriuretic response and renal impairment.

Concurrent use of aminoglycosides or cephalosporins with UpCard-CA1 may increase the risk of nephrotoxicity and ototoxicity.

The safety of UpCard-CA1 has not been evaluated in dogs with heart failure caused by etiologies other than MMVD. The safe use of UpCard-CA1 has not been evaluated in dogs with congenital heart defects.

The safe use of UpCard-CA1 has not been evaluated in dogs with diabetes mellitus or other serious metabolic diseases.

The safe use of UpCard-CA1 has not been evaluated in dogs used for breeding, or pregnant or lactating bitches.

The dose of UpCard-CA1 may need to be adjusted when administering UpCard-CA1 with digoxin.

UpCard-CA1 may potentially induce an allergic reaction in dogs with sulfonamide allergy.

UpCard-CA1 can reduce renal excretion of salicylates, leading to an increased risk of aspirin toxicity.

Adverse Reactions:

In a multi-site European clinical field study, 251 client-owned dogs suffering from edema secondary to congestive heart failure were treated with at least one dose of a tablet formulation of torsemide (n=126) or furosemide (n=125) for a 3-month treatment period. A greater overall frequency of adverse reactions was recorded in the torsemide group (n=184 events) compared with furosemide treated dogs (n=104 events).

The most common adverse reactions associated with torsemide administration involved the urinary system, including polyuria and polydipsia, renal insufficiency, increased BUN and serum creatinine, and urinary incontinence. These findings were noted at greater frequency in torsemide-treated dogs than in the furosemide treatment group.

A relative increase in the risk of serious adverse events due to renal insufficiency (including increased BUN, increased serum creatinine, and renal failure) was observed among torsemide-treated dogs compared with furosemide-treated dogs. Median BUN and serum creatinine levels were greater across all time points in torsemide-treated dogs, and were still high in this group on day 84.

Electrolyte disturbances, including hypokalemia, hypochloremia, hypercalcemia, and hypomagnesemia, were also associated with torsemide therapy. Diarrhea, vomiting, inappetence, and lethargy were also noted in torsemide-treated dogs.

Clinical findings associated with the worsening of congestive heart failure were noted in torsemide-treated dogs, including cough, dyspnea, pulmonary edema, and cardiac arrest.

A total of 30 dogs died during the study, 12 in the torsemide group and 18 in the furosemide group. Euthanasia was the most common cause of death with similar frequency between the treatment groups, and was due to progression of renal failure, deterioration of condition, acute pulmonary edema, acute cardiac death, accidental death, death from another disease condition, or unknown cause.

Contact Information:

To report suspected adverse events or to request a copy of the Safety Data Sheet (SDS), please call Vetoquinol USA, Inc. at 1-800-835-9496. For additional information about adverse drug experience reporting for animal drugs, contact FDA at 1-888-FDA-VETS or at www.fda.gov/reportanimalae.

Clinical Pharmacology:

MECHANISM OF ACTION

Mode of Action: Torsemide is secreted into the tubule lumen via the probenecid sensitive organic acid transport system. The main site of action is the medullary portion of the ascending limb of the loop of Henle. Loop diuretics mainly inhibit the Na+/2Cl-/K+ carrier from the luminal side of the cell.

Inhibition of sodium and chloride ion reabsorption not only results in saluresis but also a decrease in interstitial osmolarity within the renal medulla. This in turn decreases free water reabsorption resulting in increased water excretion/urine production.

PHARMACOKINETICS

Pharmacokinetics: In dogs, after a single intravenous dose at 0.1 mg/kg, the total body clearance was 0.017 L/h∙kg, the volume of distribution was 0.14 L/kg and the terminal half-life was 7.0 hours. The pharmacokinetic parameters following a single dose of the oral solution at 0.1 mg/kg, are presented in Table 1. Torsemide is highly bound to plasma proteins (approximately 98%). A large proportion of the dose (between 61% and 70%) is excreted in the urine as unchanged parent drug. Two metabolites (a dealkylated and a hydroxylated metabolite) were also identified in urine. For the oral solution, dose proportionality was established within the dose range of 0.4 to 0.8 mg/kg. After 14 repeated daily administrations, accumulation was minimal (geometric mean accumulation ratio = 1.11) with steady state being reached after the second administration.

Feeding significantly increased torsemide area under the curve from the time of dosing to the last quantifiable concentration (AUC) by 24% on average but no significant impact on Cmax was detected. When 2 dogs were fed wet food, Tmax was delayed (i.e., 4 h for wet food vs 0.9 h for dry food or fasted).

Table 1. Mean plasma pharmacokinetics for torsemide after a single administration of UpCard-CA1
Parameter | Torsemide (mean ± SD)
Cmax (µg/mL) | 1.21 ± 0.18
Tmax (h) | 0.75 ± 0.26
AUC0-inf (µg∙h/mL) | 7.50 ± 1.62
t1/2 (h) | 7.83 ± 1.58
Bioavailability | 96%
Cmax = maximum plasma concentration
Tmax = time to maximum plasma concentration
AUC0-inf = area under the plasma concentration time curve from time 0 extrapolated to infinity
t1/2 = apparent terminal elimination half life

Reasonable Expectation of Effectiveness:

A reasonable expectation of effectiveness may be demonstrated based on evidence such as, but not limited to, pilot data in the target species or studies from published literature.

UpCard-CA1 is conditionally approved pending a full demonstration of effectiveness.

Additional information for Conditional Approvals can be found at www.fda.gov/animalca.

Reasonable expectation of effectiveness for the management of pulmonary edema related to congestive heart failure in dogs with MMVD is based on the results from a randomized multi-site European field safety and effectiveness study using torsemide tablets. Of a total of 251 dogs that were enrolled in the study, 61 dogs with MMVD were considered appropriate for evaluation of the primary endpoint to support reasonable expectation of effectiveness because they were clinically stable and had received furosemide for at least 10 days prior to enrollment. After enrollment, 25 of these dogs were transitioned to torsemide tablets, and 36 dogs continued to be treated with furosemide.

The primary endpoint was response rate at Day 84; a dog was considered to have a successful response to treatment if pulmonary edema and/or pleural effusion or ascites had not increased compared to Day 0. The success rates were 96.0% (24/25) for the torsemide group and 80.6% (29/36) for the furosemide group.

A pharmacokinetic study compared torsemide plasma exposure and urine excretion after a single administration of torsemide tablets and UpCard-CA1 (torsemide oral solution) at 0.1 mg/kg. The relative bioavailability in plasma and urine of UpCard-CA1 were high, although the plasma Cmax and AUC values reached after administration of UpCard-CA1 were slightly lower compared to the tablets. Therefore, similar diuretic activity and safety profiles are expected following administration of each formulation.

Target Animal Safety:

In a laboratory safety study, 32 healthy, 6-month-old beagle dogs (16 males and 16 females) were randomly assigned to a placebo control group or were dosed orally once daily for 6 months with UpCard-CA1 at doses of 0.25×, 1×, and 1.5× the maximum daily recommended therapeutic dose (0.11, 0.44, 0.66 mg/kg/day, respectively).

UpCard-CA1 administration resulted in decreased food consumption and dose dependent lower body weight compared to the control group, with the 0.25×, 1×, and 1.5× torsemide groups showing a 4.6%, 9.4% and 11.8% reduction in body weight, respectively. In the 1× and 1.5× torsemide groups, increased urinary output and decreased urine specific gravity were observed. Occasional dehydration and reduced activity/lethargy were also observed in some animals.

UpCard-CA1 administration at 1× and 1.5× resulted in clinical pathology changes consistent with the expected effects of a loop diuretic: erythroid changes consisted of increased red cell mass parameters (i.e., red blood cell count, hemoglobin, and hematocrit) and serum chemistry changes consisted of increased albumin, BUN, and creatinine, and decreased chloride and potassium. These changes are consistent with dehydration secondary to diuresis and the effect of torsemide on the kidneys. UpCard-CA1 treatment had no observed effects on ophthalmologic examination findings, electrocardiography, blood pressure, and body temperature. Concentrations of torsemide increased in an approximate dose proportional manner between 0.11 and 0.66 mg/kg. At the 1× dosage, accumulation was minimal with steady state being reached by, or before, the fourth week of dosing.

Supporting Safety Study: In a second laboratory safety study, 32 healthy, 4 to 5-month-old beagle dogs (16 males and 16 females) were randomly assigned to a placebo control group or were dosed orally once daily for 13 weeks with torsemide tablets at doses of 0.23×, 0.68×, and 1.36× the maximum recommended therapeutic dose (0.1, 0.3 and 0.6 mg/kg, respectively). Water consumption increased in the group administered 0.6 mg/kg compared to the control group. Clinical observations attributed to product administration included erythema of the inner pinnae, the frequency of which increased in a dose-dependent manner.

Changes in clinical pathology were observed as follows: increased hematocrit, BUN, creatinine, and albumin concentrations; decreased plasma potassium, chloride, phosphate, and magnesium concentrations; and increased serum aldosterone levels. There were increases in urine volume, which were accompanied by reductions in specific gravity and urine concentrations of creatinine, sodium, potassium, chloride, and phosphate, and increases in the fractional excretion of calcium and phosphate. These changes appeared to be dose dependent. On necropsy, kidney weights were significantly higher in the 0.6 mg/kg group compared to the control group. Histopathological changes to the renal cortex and medulla were minimal to mild. Systemic exposure (AUClast) increased in a dose proportional manner between 0.1 and 0.6 mg/kg. Accumulation was minimal with steady state being reached by, or before, the fourth week of dosing.

Storage:

Store at or below 30°C (86°F). Excursions permitted between 4°C and 40°C (39°F and 104°F). Discard 90 days after opening.

How Supplied:

UpCard®-CA1 (torsemide oral solution) is supplied at a concentration of 0.2% (2 mg) torsemide per mL.

UpCard®-CA1 is supplied in bottle sizes of 32 mL and 96 mL.

Manufactured for
Vetoquinol USA, Inc.
4250 N. Sylvania Ave
Fort Worth, TX 76137

Made in
Canada by
Vetoquinol N. A. Inc.
Princeville, Québec, Canada

1 14DEC2023

104055

Vetoquinol, the Vetoquinol logo, and UpCard are trademarks of Vetoquinol S.A. ©2023 Vetoquinol USA, Inc.

PRINCIPAL DISPLAY PANEL - 32 mL Bottle Label

NDC 17030-020-32

UpCard®-CA1
(torsemide oral solution)
2 mg/mL
Diuretic for oral use in dogs only.

Conditionally approved by FDA pending
a full demonstration of effectiveness
under application number 141-577.

It is a violation of Federal law to use this
product other than as directed in the labeling.

CAUTION: Federal law restricts this drug to use
by or on the order of a licensed veterinarian.

Net Contents: 32 mL

vetoquinol